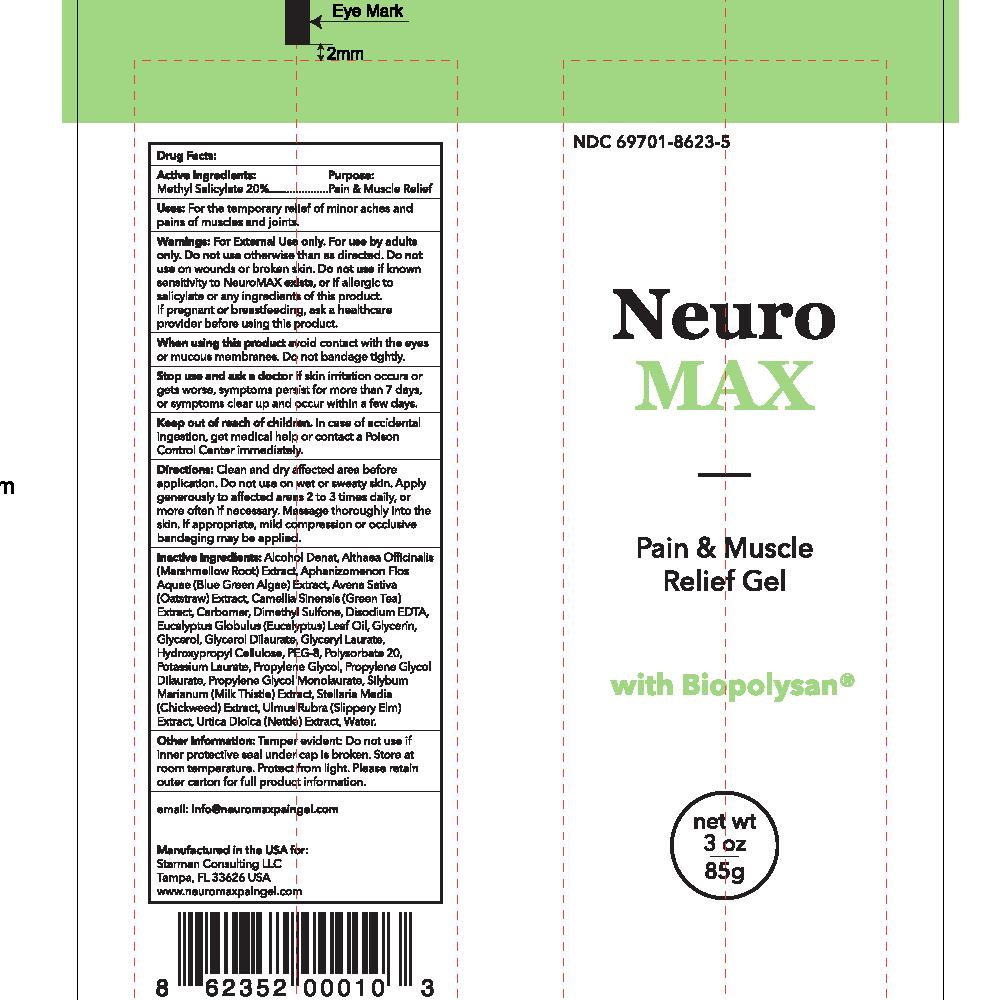 DRUG LABEL: Neuro Max Pain and Muscle Relief Gel
NDC: 69701-8623 | Form: LOTION
Manufacturer: Starman Consulting LLC
Category: otc | Type: HUMAN OTC DRUG LABEL
Date: 20150623

ACTIVE INGREDIENTS: METHYL SALICYLATE 20 g/100 g
INACTIVE INGREDIENTS: ALCOHOL 31 g/100 g; ALTHAEA OFFICINALIS ROOT .1 g/100 g; APHANIZOMENON FLOS-AQUAE .1 g/100 g; AVENA SATIVA LEAF .1 g/100 g; CAMELLIA SINENSIS FLOWER .1 g/100 g; EUCALYPTUS GLOBULUS LEAF .6 g/100 g; SILYBUM MARIANUM LEAF .1 g/100 g; STELLARIA MEDIA LEAF .1 g/100 g; ULMUS RUBRA BARK .1 g/100 g; URTICA DIOICA LEAF .1 g/100 g; CARBOMER 940 .8 g/100 g; DIMETHYL SULFONE 2.4 g/100 g; DISODIUM HEDTA .05 g/100 g; GLYCERIN 9 g/100 g; GLYCERYL DILAURATE 1 g/100 g; GLYCERYL LAURATE 1 g/100 g; HYDROXYPROPYL CELLULOSE (TYPE M) 1 g/100 g; POLYETHYLENE GLYCOL 400 10 g/100 g; POLYSORBATE 20 4.5 g/100 g; WATER 16.85 g/100 g

Neuro Max Pain and Muscle Relief Gel

PURPOSE

Pain & Muscle Relief

Uses:

For the temporary relief of minor aches and pains of muscles and joints.

WARNINGS

For External Use only. For use by adults only.

Do not use otherwise than as directed. Do not use on wounds or broken skin. Do not use if known sensitivity to NeuroMAX exists, or if allergic to salicylate or any ingredients of this product

PREGNANCY OR BREAST FEEDING

If pregnant or breastfeeding, ask a healthcare provider before using this product

When using this product avoid contact with the eyes or mucous membranes. Do not bandage tightly.

Stop use and ask a doctor if skin irritation occurs or gets worse, symptoms persist for more than 7 days, or symptoms clear up and occur within a few days.

Keep out of reach of children. In case of accidental ingestion, get medical help or contact a Poison Control Center immediately.

INACTIVE INGREDIENT

Inactive Ingredients: Alcohol Denat, Althaea Officinalis (Marshmellow Root) Extract, Aphanizomenon Flos Aquae (Blue Green Algae) Extract, Avena Sativa (Oatstraw) Extract, Camellia Sinensis (Green Tea) Extract, Carbomer, Dimethyl Sulfone, Disodium EDTA, Eucalyptus Globulus (Eucalyptus) Leaf Oil, Glycerin, Glycerol, Glycerol Dilaurate, Glyceryl Laurate, Hydroxypropyl Cellulose, PEG-8, Polysorbate 20, Potassium Laurate, Propylene Glycol, Propylene Glycol Dilaurate, Propylene Glycol Monolaurate, Silybum Marianum (Milk Thistle) Extract, Stellaria Media (Chickweed) Extract, Ulmus Rubra (Slippery Elm) Extract, Urtica Dioica (Nettle) Extract, Water.

Other Information: Tamper evident: Do not use if inner protective seal under cap is broken. Store at room temperature. Protect from light. Please retain outer carton for full product information.

Questions? email info@neuromaxpaingel.com